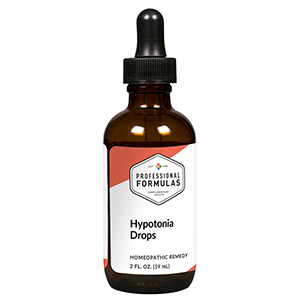 DRUG LABEL: Hypotonia Drops
NDC: 63083-2030 | Form: LIQUID
Manufacturer: Professional Complementary Health Formulas
Category: homeopathic | Type: HUMAN OTC DRUG LABEL
Date: 20190815

ACTIVE INGREDIENTS: HAWTHORN LEAF WITH FLOWER 1 [hp_X]/59 mL; ASIAN GINSENG 2 [hp_X]/59 mL; CYTISUS SCOPARIUS FLOWERING TOP 3 [hp_X]/59 mL; PRUNUS LAUROCERASUS LEAF 3 [hp_X]/59 mL; NERIUM OLEANDER WHOLE 4 [hp_X]/59 mL; SUS SCROFA ADRENAL GLAND 6 [hp_X]/59 mL; BEEF KIDNEY 6 [hp_X]/59 mL; ANGIOTENSIN I 12 [hp_X]/59 mL
INACTIVE INGREDIENTS: ALCOHOL; WATER

C30

ACTIVE INGREDIENTS

Crataegus oxyacantha 1X
Panax ginseng 2X
Cytisus scoparius 3X
Laurocerasus 3X
Oleander 4X
Adrenal 6X
Kidney 6X
Angiotensin 12X

QUESTIONS

Professional Formulas

PO Box 2034 Lake Oswego, OR 97035

INDICATIONS

For the temporary relief of dizziness, fatigue, nausea, weakened memory, or slow perception.*

PURPOSE

*Claims based on traditional homeopathic practice, not accepted medical evidence. Not FDA evaluated.

WARNINGS

Consult a doctor if condition worsens or if symptoms persist. Keep out of the reach of children. In case of overdose, get medical help or contact a poison control center right away. If pregnant or breastfeeding, ask a healthcare professional before use.

Keep out of the reach of children.

PREGNANCY OR BREAST FEEDING

If pregnant or breastfeeding, ask a healthcare professional before use.

DIRECTIONS

Place drops under tongue 30 minutes before/after meals. Adults and children 12 years and over: Take 10 drops up to 3 times per day. Consult a physician for use in children under 12 years of age.

OTHER INFORMATION

Tamper resistant. If seal is broken, do not use. After opening, close container tightly and store at room temperature away from heat.

INACTIVE INGREDIENTS

20% ethanol, purified water.

LABEL

Est 1985

Professional Formulas

Complementary Health

Hypotonia Drops

Homeopathic Remedy

2 FL. OZ. (59 mL)